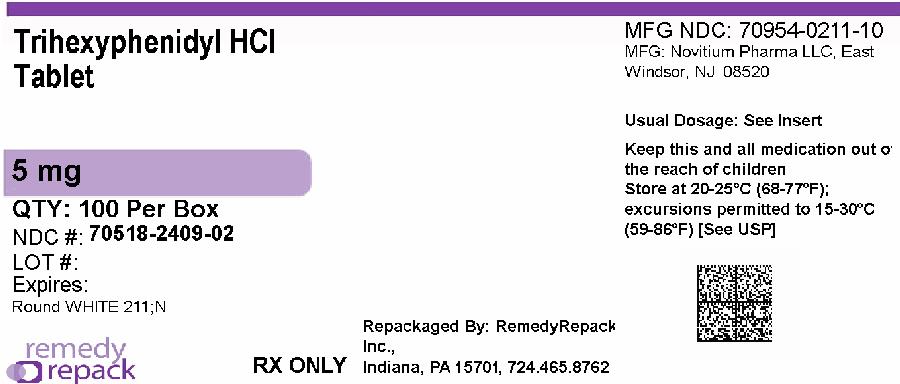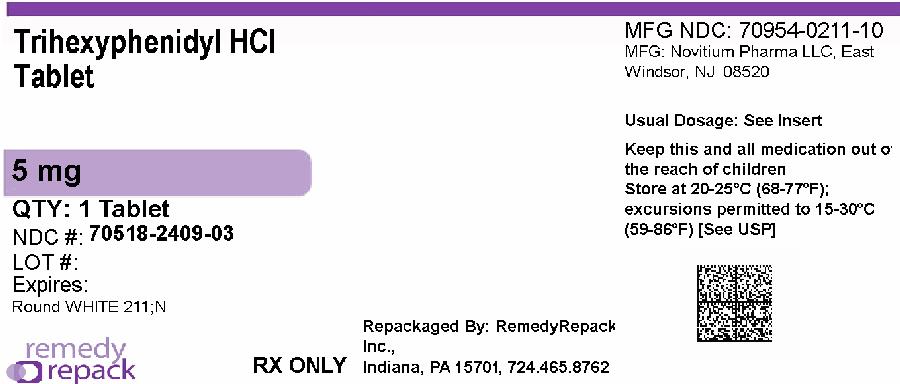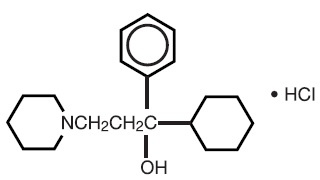 DRUG LABEL: TRIHEXYPHENIDYL HYDROCHLORIDE
NDC: 70518-2409 | Form: TABLET
Manufacturer: REMEDYREPACK INC.
Category: prescription | Type: HUMAN PRESCRIPTION DRUG LABEL
Date: 20260205

ACTIVE INGREDIENTS: TRIHEXYPHENIDYL HYDROCHLORIDE 5 mg/1 1
INACTIVE INGREDIENTS: MICROCRYSTALLINE CELLULOSE; MAGNESIUM STEARATE; SODIUM STARCH GLYCOLATE TYPE A POTATO

Novitium Pharma LLC.
TRIHEXYPHENIDYL HYDROCHLORIDE Tablets, USP 2 mg and 5 mg
Rx Only

DESCRIPTION

Trihexyphenidyl hydrochloride Tablets, USP is a synthetic antispasmodic drug available in the following forms: Tablets, 2 mg and 5 mg. It is designated chemically 1-Piperidinepropanol,α-cyclohexyl-α-phenyl-, hydrochloride. The structural formula is represented below:

Trihexyphenidyl Hydrochloride Tablets, USP 2 mg and 5 mg contain the following inactive ingredients: Microcrystalline cellulose, magnesium stearate and sodium starch glycolate.

CLINICAL PHARMACOLOGY

Trihexyphenidyl Hydrochloride is the substituted piperidine salt, 3-(1-piperidyl)- 1-phenylcyclohexyl-1-propanol hydrochloride, which exerts a direct inhibitory effect upon the parasympathetic nervous system. It also has a relaxing effect on smooth musculature; exerted both directly upon the muscle tissue itself and indirectly through an inhibitory effect upon the parasympathetic nervous system. Its therapeutic properties are similar to those of atropine, although undesirable side effects are ordinarily less frequent and severe than with the latter.

INDICATIONS & USAGE

This drug is indicated as an adjunct in the treatment of all forms of parkinsonism (postencephalitic, arteriosclerotic, and idiopathic). It is often useful as adjuvant therapy when treating these forms of parkinsonism with levodopa. Additionally, it is indicated for the control of extrapyramidal disorders caused by central nervous system drugs such as the dibenzoxazepines, phenothiazines, thioxanthenes, and butyrophenones.

WARNINGS

Patients to be treated with trihexyphenidyl hydrochloride should have a gonioscope evaluation and close monitoring of intraocular pressures at regular periodic intervals.

PRECAUTIONS

GENERAL PRECAUTIONS

Although trihexyphenidyl hydrochloride is not contraindicated for patients with cardiac, liver, or kidney disorders, or with hypertension, such patients should be maintained under close observation.

Since the use of trihexyphenidyl hydrochloride may, in some cases, continue indefinitely and since it has atropine- like properties, patients should be subjected to constant and careful long-term observation to avoid allergic and other untoward reactions. In as much as trihexyphenidyl hydrochloride possesses some parasympatholytic activity, it should be used with caution in patients with glaucoma, obstructive disease of the gastrointestinal or genitourinary tracts, and in elderly males with possible prostatic hypertrophy.

Geriatric patients, particularly over the age of 60, frequently develop increased sensitivity to the actions of drugs of this type, and hence, require strict dosage regulation. Incipient glaucoma may be precipitated by parasympatholytic drugs such as trihexyphenidyl hydrochloride.

Tardive dyskinesia may appear in some patients on long term therapy with antipsychotic drugs or may occur after therapy when these drugs have been discontinued. Antiparkinson agents do not alleviate the symptoms of tardive dyskinesia and in some instances may aggravate them. However, parkinsonism and tardive dyskinesia often coexist in patients receiving chronic neuroleptic treatment, and anticholinergic therapy with trihexyphenidyl hydrochloride may relieve some of these parkinsonism symptoms.

ADVERSE REACTIONS

Minor side effects, such as dryness of the mouth, blurring of vision, dizziness, mild nausea, or nervousness, will be experienced by 30 to 50 percent of all patients. These sensations, however, are much less troublesome with trihexyphenidyl hydrochloride than with belladonna alkaloids and are usually less disturbing than unalleviated parkinsonism. Such reactions tend to become less pronounced, and even to disappear, as treatment continues. Even before these reactions have remitted spontaneously, they may often be controlled by careful adjustment of the dosage form, amount of drug, or interval between doses.

Isolated instances of suppurative parotitis secondary to excessive dryness of the mouth, skin rashes, dilatation of the colon, paralytic ileus, and certain psychiatric manifestations such as delusions and hallucinations, plus one doubtful case of paranoia all of which may occur with any of the atropine-like drugs, have been rarely reported with trihexyphenidyl hydrochloride.

Patients with arteriosclerosis or with a history of idiosyncrasy to other drugs may exhibit reactions of mental confusion, agitation, disturbed behavior, or nausea and vomiting. Such patients should be allowed to develop a tolerance through the initial administration of a small dose and gradual increase in dose until an effective level is reached. If a severe reaction should occur, administration of the drug should be discontinued for a few days and then resumed at a lower dosage. Psychiatric disturbances can result from indiscriminate use (leading to overdosage) to sustain continued euphoria.
Potential side effects associated with the use of any atropine-like drugs include constipation, drowsiness, urinary hesitancy or retention, tachycardia, dilation of the pupil, increased intraocular tension, weakness, vomiting, and headache.

The occurrence of angle-closure glaucoma due to long-term treatment with trihexyphenidyl hydrochloride has been reported.

To report SUSPECTED ADVERSE REACTIONS, contact Novitium Pharma LLC at 1-516-305-1658 or FDA at 1-800-FDA-1088 or www.fda.gov/medwatch.

DOSAGE & ADMINISTRATION

Dosage should be individualized. The initial dose should be low and then increased gradually, especially in patients over 60 years of age. Whether trihexyphenidyl hydrochloride may best be given before or after meals should be determined by the way the patient reacts. Postencephalitic patients, who are usually more prone to excessive salivation, may prefer to take it after meals and may, in addition, require small amounts of atropine which, under such circumstances, is sometimes an effective adjuvant. If trihexyphenidyl hydrochloride tends to dry the mouth excessively, it may be better to take it before meals, unless it causes nausea. If taken after meals, the thirst sometimes induced can be allayed by mint candies, chewing gum or water.

Trihexyphenidyl Hydrochloride in Idiopathic Parkinsonism

As initial therapy for parkinsonism, 1 mg may be administered the first day. The dose may then be increased by 2 mg increments at intervals of three to five days, until a total of 6 to 10 mg is given daily. The total daily dose will depend upon what is found to be the optimal level. Many patients derive maximum benefit from this daily total of 6 to 10 mg, but some patients, chiefly those in the postencephalitic group, may require a total daily dose of 12 to 15 mg.

Trihexyphenidyl Hydrochloride in Drug-Induced Parkinsonism

The size and frequency of dose of trihexyphenidyl hydrochloride needed to control extrapyramidal reactions to commonly employed tranquilizers, notably the phenothiazines, thioxanthenes, and butyrophenones, must be determined empirically. The total daily dosage usually ranges between 5 and 15 mg, although, in some cases, these reactions have been satisfactorily controlled on as little as 1 mg daily. It may be advisable to commence therapy with a single 1 mg dose. If the extrapyramidal manifestations are not controlled in a few hours, the subsequent doses may be progressively increased until satisfactory control is achieved. Satisfactory control may sometimes be more rapidly achieved by temporarily reducing the dosage of the tranquilizer on instituting trihexyphenidyl hydrochloride therapy and then adjusting dosage of both drugs until the desired ataractic effect is retained without onset of extrapyramidal reactions.

It is sometimes possible to maintain the patient on a reduced trihexyphenidyl hydrochloride dosage after the reactions have remained under control for several days. Instances have been reported in which these reactions have remained in remission for long periods after trihexyphenidyl hydrochloride therapy was discontinued.

Concomitant Use of Trihexyphenidyl Hydrochloride with Levodopa

When trihexyphenidyl hydrochloride is used concomitantly with levodopa, the usual dose of each may need to be reduced. Careful adjustment is necessary, depending on side effects and degree of symptom control. Trihexyphenidyl hydrochloride dosage of 3 to 6 mg daily, in divided doses, is usually adequate.

Concomitant Use of Trihexyphenidyl Hydrochloride with Other Parasympathetic Inhibitors

Trihexyphenidyl Hydrochloride may be substituted, in whole or in part, for other parasympathetic inhibitors. The usual technique is partial substitution initially, with progressive reduction in the other medication as the dose of trihexyphenidyl hydrochloride is increased.

Trihexyphenidyl Hydrochloride Tablets - The total daily intake of trihexyphenidyl hydrochloride tablets is tolerated best if divided into 3 doses and taken at mealtimes. High doses (> 10 mg daily) may be divided into 4 parts, with 3 doses administered at meal times and the fourth at bedtime.

HOW SUPPLIED

Trihexyphenidyl Hydrochloride Tablets, USP 5 mg are available as white, flat face, beveled edge and round. The upper layer is bisected and debossed "211/N", the lower layer is plain:

NDC: 70518-2409-00

NDC: 70518-2409-01

NDC: 70518-2409-02

NDC: 70518-2409-03

NDC: 70518-2409-04

PACKAGING: 100 in 1 BOX

PACKAGING: 1 in 1 POUCH

PACKAGING: 100 in 1 BOX

PACKAGING: 1 in 1 POUCH

PACKAGING: 30 in 1 BLISTER PACK

Dispense in a tight container with child-resistant closure.
Store at 20° to 25° (68° to 77°F) [See USP Controlled Room Temperature].

Repackaged and Distributed By:

Remedy Repack, Inc.

625 Kolter Dr. Suite #4 Indiana, PA 1-724-465-8762

PACKAGE LABEL

DRUG: TRIHEXYPHENIDYL HYDROCHLORIDE

GENERIC: TRIHEXYPHENIDYL HYDROCHLORIDE

DOSAGE: TABLET

ADMINSTRATION: ORAL

NDC: 70518-2409-0

NDC: 70518-2409-1

NDC: 70518-2409-2

NDC: 70518-2409-3

NDC: 70518-2409-4

COLOR: white

SHAPE: ROUND

SCORE: Two even pieces

SIZE: 10 mm

IMPRINT: 211;N

OUTER PACKAGING: 100 in 1 BOX

PACKAGING: 1 in 1 POUCH

OUTER PACKAGING: 100 in 1 BOX

PACKAGING: 1 in 1 POUCH

PACKAGING: 30 in 1 BLISTER PACK

ACTIVE INGREDIENT(S):

- TRIHEXYPHENIDYL HYDROCHLORIDE 5mg in 1

INACTIVE INGREDIENT(S):

- MAGNESIUM STEARATE
- MICROCRYSTALLINE CELLULOSE
- SODIUM STARCH GLYCOLATE TYPE A POTATO